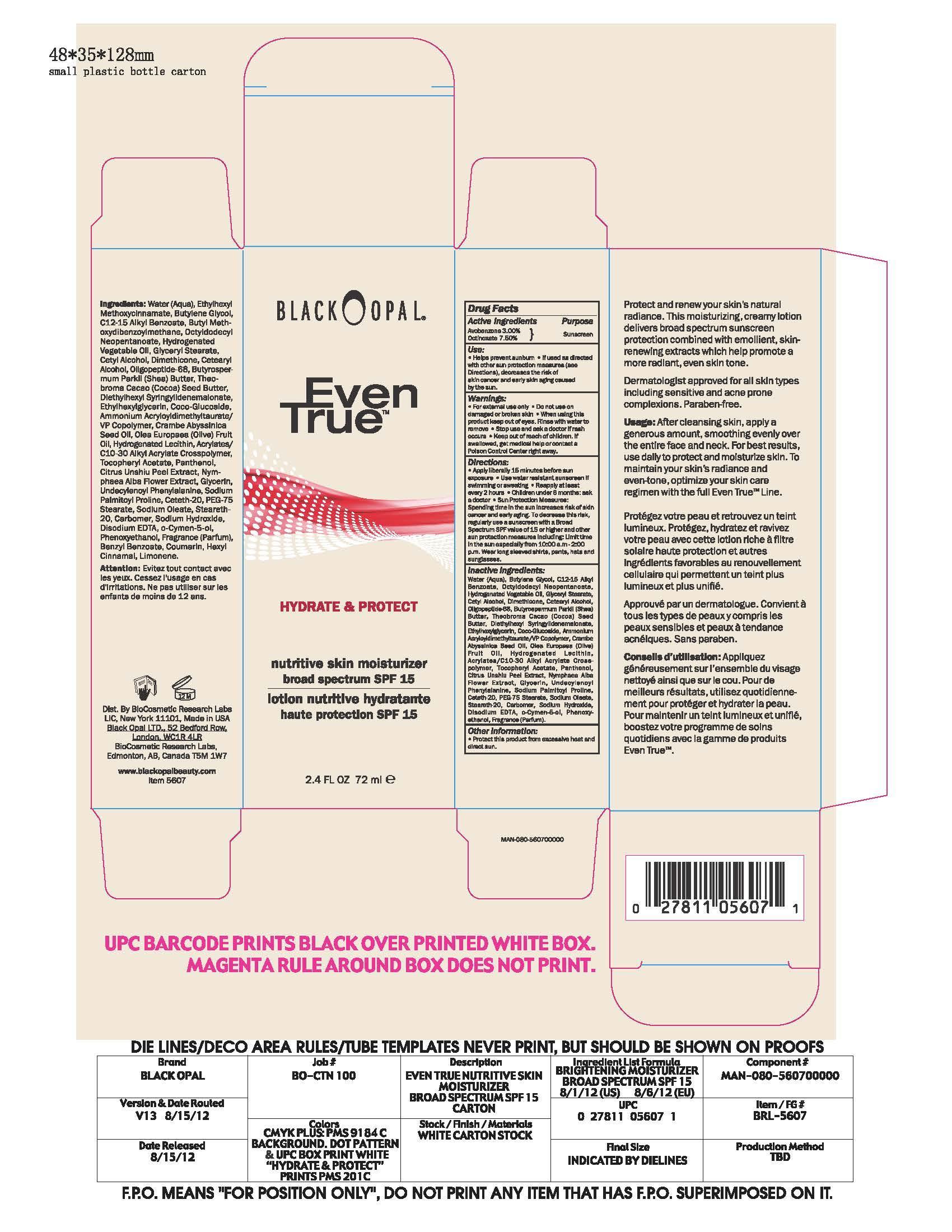 DRUG LABEL: BO SPF15
NDC: 59735-100 | Form: LOTION
Manufacturer: Mana Products
Category: otc | Type: HUMAN OTC DRUG LABEL
Date: 20130927

ACTIVE INGREDIENTS: AVOBENZONE 3 g/100 g; Octinoxate 7.5 g/100 g
INACTIVE INGREDIENTS: WATER; BUTYLENE GLYCOL; C12-15 ALKYL BENZOATE; OCTYLDODECYL NEOPENTANOATE; GLYCERYL STEARATE SE; CETYL ALCOHOL; DIMETHICONE; SHEA BUTTER; COCOA BUTTER; DIETHYLHEXYL SYRINGYLIDENEMALONATE; ETHYLHEXYLGLYCERIN; COCO-GLYCERIDES; AMMONIUM ACRYLOYLDIMETHYLTAURATE/VP COPOLYMER; CRAMBE HISPANICA SUBSP. ABYSSINICA SEED OIL; OLEA EUROPAEA FLOWER; HYDROGENATED SOYBEAN LECITHIN; (C10-C30)ALKYL METHACRYLATE ESTER; .ALPHA.-TOCOPHEROL ACETATE; PANTHENOL; NYMPHAEA ALBA FLOWER; GLYCERIN; SODIUM PALMITOYL PROLINE; CETETH-20; PEG-75 STEARATE; SODIUM OLEATE; STEARETH-20; CARBOMER 940; SODIUM HYDROXIDE; DISODIUM EDTA-COPPER; O-CYMEN-5-OL; PHENOXYETHANOL

DRUG FACTS

Active Ingredients

Avobenzone 3.00%
Octinoxate 7.50%

Use

- Helps prevens sunburn
- If used as direced with other sun protection measures (see Directions), decreases the risk of skin cancer and early skin again caused by the sun.

Warnings

- For external use only
- Do not use on damaged or broken skin
- When using this product keep out of eyes. Rinse with water to remove
- Stop use and ask a docor if rash occurs
- Keep out of reach of children. If swalled, get medical help or contact a Poison Control Center right away.

Directions

- Apply liberally 15 minutes before sun exposure
- Use water resistant sunscreen if swimming or sweathing
- Reapply at least every 2 hours
- Children under 6 months: ask a doctor
- Sun Protection Measures: Spending time in the sun decreases risk of skin cancer and early again. To decrease this risk, regulaory use a sunscreen with a Broad Spectrum SPF value of 15 or higher and other sun protection measures including: Limit time in the sun especially from 10:00 am - 2:00 pm. Wear long sleeved shirts, pants, hats and sunglasses.

Inactive Ingredients

Water (Aqua), Butylene Glycol, C12-15 Alkyl Benzoate, Octyldodecyl Neopentanoate, Hydrogenated Vegetable Oil, Glyceryl Stearate, Cetyl Alcohol, Dimethicone, Cetearyl Alcohol, Oligopepetide-68, Butyrospermum Parkii (Shea) Buter, Theobroma Cacao (Cocoa) Seed Buter, Diethylhexyl Syringylidenemalonate, Ethylhexylglycerin, Coco-Glucoside, Ammonium Acryloyldimethyltaurate/VP Copolyner, Crambe Abyssinica Seed Oil, Olea Europaea (Olive) Fruit Oil, Hydrogenated Lecithin, Acrylates/C10-30 Alkyl Acrylate Crosspolymer, Tocopheryl Acetate, Panthenol, Citrus Unshiu Peel Extract, Nymphaea Alba Flower Extract, Glycerin, Undecylenoyl Phenylalanine, Sodium Palmitoyl Proline, Ceteth-20, PEG-75 Stearate, Sodium Oleate, Steareth-20, Carbomer, Sodium Hydroxide, Disodium EDTA, o-Cymen-5-ol, Phenoxyethanol, Fragrance (Parfum)

Other Information

Protect this product form excessive heat and direct sun